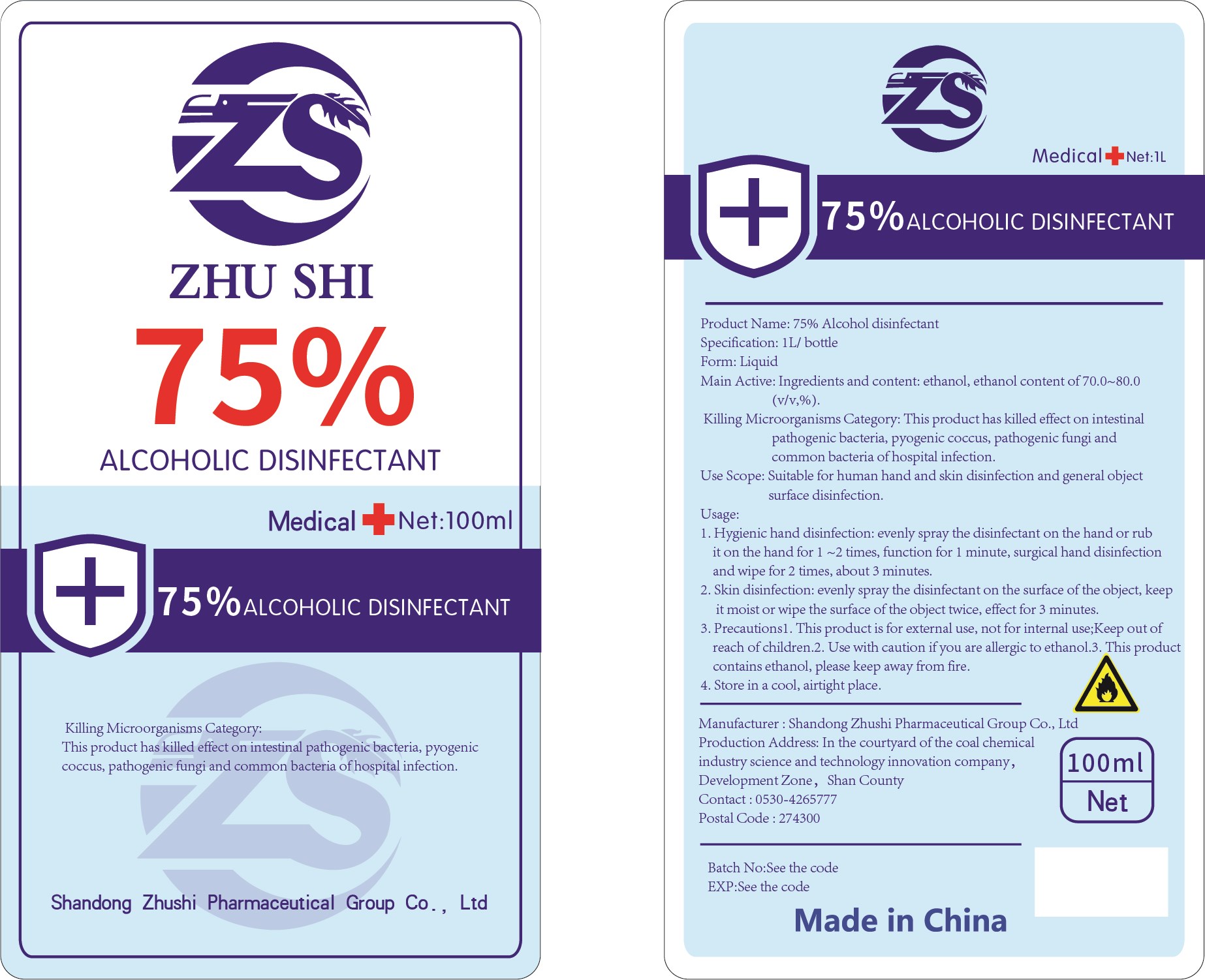 DRUG LABEL: Aoliben 75% alcohol disinfectant
NDC: 56040-005 | Form: LIQUID
Manufacturer: Shandong Zhushi Pharmaceutical Group Co., Ltd.
Category: otc | Type: HUMAN OTC DRUG LABEL
Date: 20220310

ACTIVE INGREDIENTS: ALCOHOL 78.9 mL/100 mL
INACTIVE INGREDIENTS: WATER

DOSAGE AND ADMINISTRATION

Store in a cool, airtight place.

INACTIVE INGREDIENT

Purified water

INDICATIONS AND USAGE

1. Hygienic hand disinfection: evenly spray the disinfectant on the hand or rub it on the hand for 1 ~2 times, function for 1 minute, surgical hand disinfection and wipe for 2 times, about 3 minutes.
2. Skin disinfection: evenly spray the disinfectant on the surface of the object, keep it moist or wipe the surface of the object twice, effect for 3 minutes.

ACTIVE INGREDIENT

Alcohol

keep out of reach of children

PURPOSE

Disinfection
Sterilization

WARNINGS

This product is for external use, not for internal use